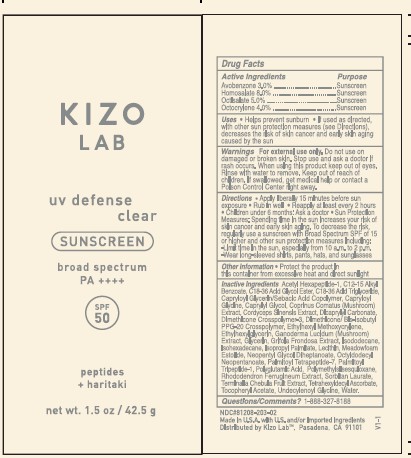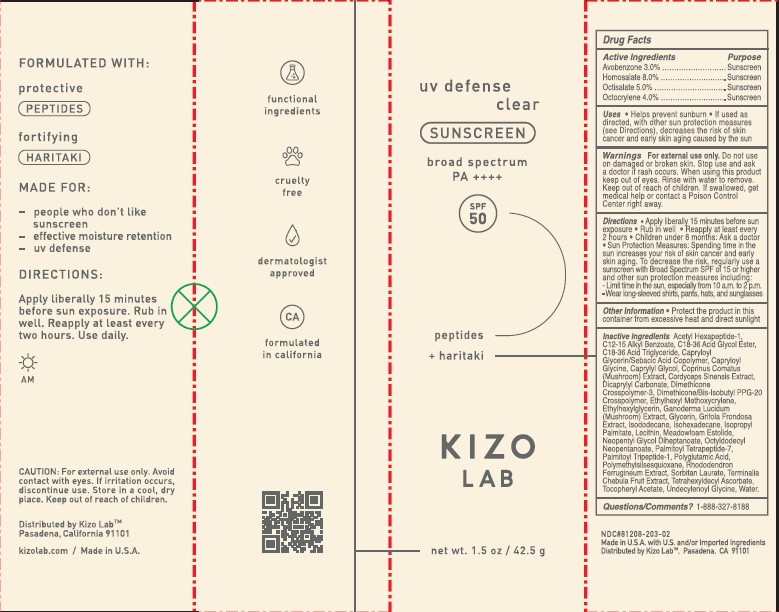 DRUG LABEL: KIZO LAB UV DEFENSE CLEAR SUNSCREN SPF50
NDC: 81208-203 | Form: GEL
Manufacturer: YB CHEMIA LLC
Category: otc | Type: HUMAN OTC DRUG LABEL
Date: 20260128

ACTIVE INGREDIENTS: HOMOSALATE 8 g/100 g; OCTOCRYLENE 4 g/100 g; AVOBENZONE 3 g/100 g; OCTISALATE 5 g/100 g
INACTIVE INGREDIENTS: CAPRYLOYL GLYCERIN/SEBACIC ACID COPOLYMER (2000 MPA.S) 1 g/100 g; CAPRYLOYL GLYCINE 1 g/100 g; CAPRYLYL GLYCOL 1 g/100 g; DIMETHICONE/BIS-ISOBUTYL PPG-20 CROSSPOLYMER 1 g/100 g; DICAPRYLYL CARBONATE 1 g/100 g; DIMETHICONE CROSSPOLYMER (450000 MPA.S AT 12% IN CYCLOPENTASILOXANE) 1 g/100 g; ETHYLHEXYL METHOXYCRYLENE 1 g/100 g; ALKYL (C12-15) BENZOATE 1 g/100 g; ISOHEXADECANE 1 g/100 g; WATER 1 g/100 g; DIMETHICONE/VINYL DIMETHICONE CROSSPOLYMER (SOFT PARTICLE) 1 g/100 g; PALMITOYL TRIPEPTIDE-1 1 g/100 g; POLYMETHYLSILSESQUIOXANE (11 MICRONS) 1 g/100 g; ISODODECANE 1 g/100 g; ISOPROPYL PALMITATE 1 g/100 g; LECITHIN, SOYBEAN 1 g/100 g; MEADOWFOAM ESTOLIDE 1 g/100 g; PALMITOYL TETRAPEPTIDE-7 1 g/100 g; UNDECYLENOYL GLYCINE 1 g/100 g; ACETYL HEXAPEPTIDE-1 1 g/100 g; C18-36 ACID TRIGLYCERIDE 1 g/100 g; ETHYLHEXYLGLYCERIN 1 g/100 g; GLYCERIN 1 g/100 g; NEOPENTYL GLYCOL DIHEPTANOATE 1 g/100 g; OCTYLDODECYL NEOPENTANOATE 1 g/100 g; TETRAHEXYLDECYL ASCORBATE 1 g/100 g

KIZO LAB UV DEFENSE CLEAR SUNSCREEN SPF50

Active Ingredients

Drug Facts

Active Ingredients ……………….….. Purpose

Avobenzone 3.0% ……………… Sunscreen

Homosalate 8.0% ……………… Sunscreen

Octisalate 5.0% ……………… Sunscreen

Octocrylene 4.0% ……………… Sunscreen

USES

Helps prevent sunburn

If used as directed, with other sun protection measures (see Directions), decreases the risk of skin cancer and early skin aging caused by the sun

WARNINGS

For external use only

Do not use on damaged or broken skin

Stop use and ask a doctor if rash occurs

When using this product keep out of eyes. Rinse with water to remove.

Keep out of reach of children. If swallowed, get medical help or contact a Poison Control Center right away.

DIRECTIONS

Apply liberally 15 minutes before sun exposure
Rub in well.
Reapply at least every 2 hours
Children under 6 months: Ask a doctor
Sun Protection Measures: Spending time in the sun increases your risk of skin cancer and early skin aging. To decrease the risk, regularly use a sunscreen with Broad Spectrum SPF of 15 or higher and other sun protection measures including:

Limit time in the sun, especially 10 a.m. to 2 p.m.
Wear long-sleeved shirts, pants, hats, and sunglasses.

OTHER INFORMATION

protect the product in this container from excessive heat and direct sunlight

Inactive Ingredients

Acetyl Hexapeptide-1, C12-15 Alkyl Benzoate, C18-36 Acid Glycol Ester, C18-36 Acid Triglyceride, Capryloyl Glycerin/Sebacic Acid Copolymer, Capryloyl Glycine, Caprylyl Glycol, Coprinus Comatus (Mushroom) Extract, Cordyceps Sinensis Extract, Dicaprylyl Carbonate, Dimethicone Crosspolymer-3, Dimethicone/Bis-Isobutyl PPG-20 Crosspolymer, Ethylhexyl Methoxycrylene, Ethylhexylglycerin, Ganoderma Lucidum (Mushroom) Extract, Glycerin, Grifola Frondosa Extract, Isododecane, Isohexadecane, Isopropyl Palmitate, Lecithin, Meadowfoam Estolide, Neopentyl Glycol Diheptanoate, Octyldodecyl Neopentanoate, Palmitoyl Tetrapeptide-7, Palmitoyl Tripeptide-1, Polyglutamic Acid, Polymethylsilsesquioxane, Rhododendron Ferrugineum Extract, Sorbitan Laurate, Terminalia Chebula Fruit Extract, Tetrahexyldecyl Ascorbate, Tocopheryl Acetate, Undecylenoyl Glycine, Water.

DESCRIPTION

KIZO LAB UV DEFENSE SPF50

Directions:

Apply liberally 15 minutes before sun exposure
Rub in well.
Reapply at least every 2 hours

Indications & Usage

Helps prevent sunburn

If used as directed, with other sun protection measures (see Directions), decreases the risk of skin cancer and early skin aging caused by the sun

PACKAGE LABEL

KIZO SPF 50 BOX